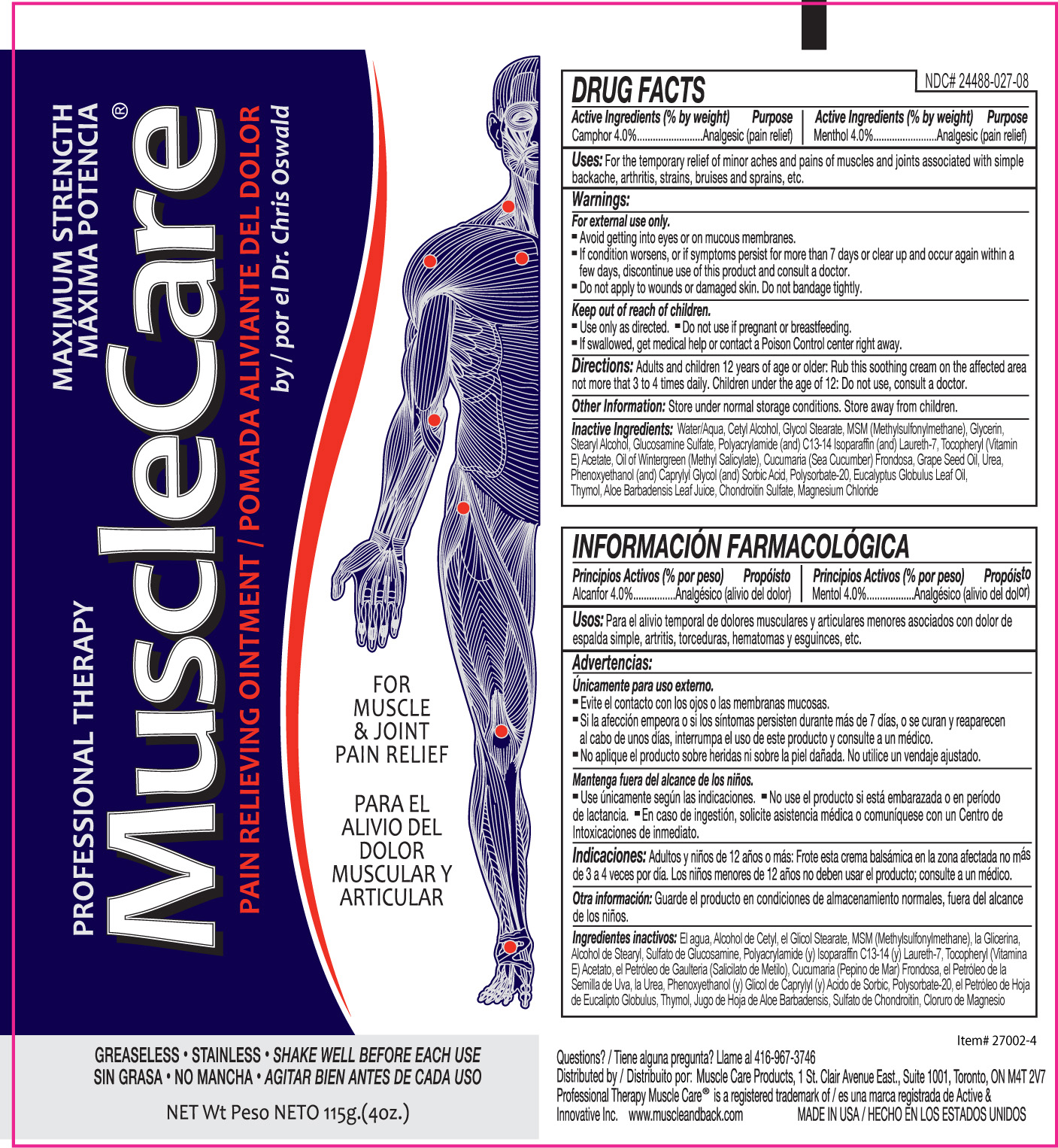 DRUG LABEL: MuscleCare
NDC: 24488-027 | Form: OINTMENT
Manufacturer: Active and Innovative
Category: otc | Type: HUMAN OTC DRUG LABEL
Date: 20110621

ACTIVE INGREDIENTS: MENTHOL 4.6 g/115 g; CAMPHOR (SYNTHETIC) 4.6 g/115 g
INACTIVE INGREDIENTS: WATER; CETYL ALCOHOL; GLYCOL STEARATE; DIMETHYL SULFONE; GLYCERIN; STEARYL ALCOHOL; GLUCOSAMINE SULFATE; ACRYLAMIDE; C13-14 ISOPARAFFIN; LAURETH-7; ALPHA-TOCOPHEROL ACETATE; METHYL SALICYLATE; CUCUMARIA FRONDOSA; GRAPE SEED OIL; UREA; PHENOXYETHANOL; SORBIC ACID; POLYSORBATE 20; EUCALYPTUS OIL; THYMOL; ALOE VERA LEAF; SULFATE ION; MAGNESIUM CHLORIDE

Drug Facts:

Active Ingredient (% by weight)

Camphor 4.0%
Menthol 4.0%

Purpose

Analgesic (pain relief)

Analgesic (pain relief)

Uses:

For the temporary relief of minor aches and pains of muscles and joints associated with simple backache, arthritis, strains, bruises and sprains, etc.

Warnings:

For external use only.

- Avoid getting into eyes or on mucous membranes.
- If condition worsens, or if symptoms persist for more than 7 days or clear up and occur again within a few days, discontinue use of this product and consult a doctor.
- Do not apply to wounds or damaged skin. Do not bandage tightly.

Keep out of reach of children.

- Use only as directed
- Do not use if pregnant or breastfeeding
- If swallowed, get medical help or contact a Poison Control center right away

Directions:

Adults and children 12 years of age or older: Rub this soothing cream on the affected area not more than 3 to 4 times daily. Children under the age of 12: Do not use, consult a doctor.

Other Information:

Store under normal storage conditions. Store away from children.

Inactive Ingredients:

Water/Aqua; Cetyl Alcohol, Glycol Stearate, MSM (Methylsulfonylmethane), Glycerin, Stearyl Alcohol, Glucosamine Sulfate, Polyacrylamide (and) C13-14 Isoparaffin (and) Laureth-7, Tocopheryl (Vitamain E) Acetate, Oil of Wintergreen (Methyl Salicylate), Cucumaria (Sea Cucumber) Frondosa, Grape Seed Oil, Urea, Phenoxyethanol (and) Caprylyl Glycol (and) Sorbic Acid, Polysorbate-20, Eucalyptus Globulus Leaf Oil, Thymol, Aloe Barbadensis Leaf Juice, Chondroitin Sulfate, Magnesium Chloride

Questions?/Tiene alguna pregunta?

Llame al 416-967-3746

PACKAGE LABEL

Placeholder Text